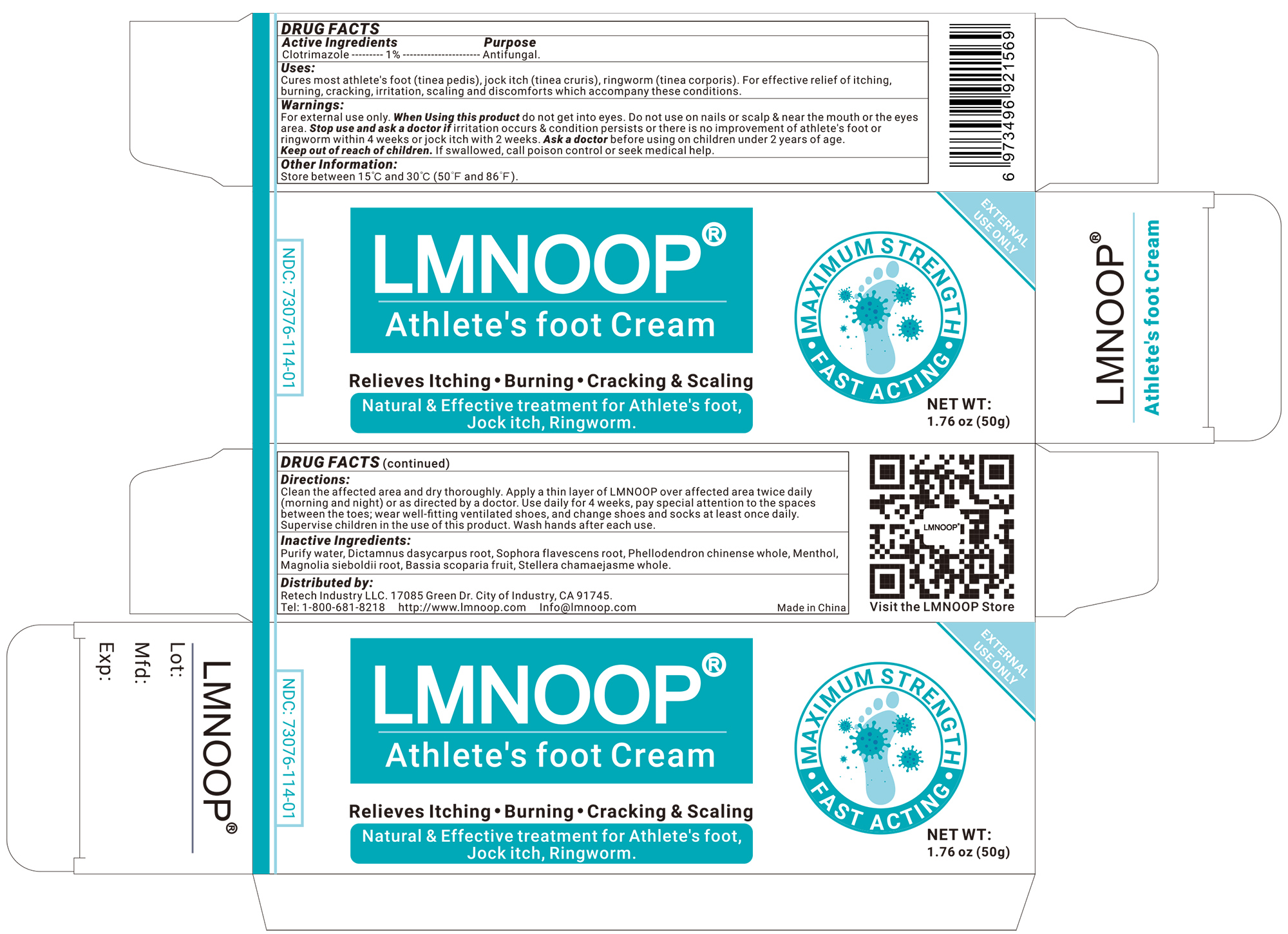 DRUG LABEL: LMNOOP Athletes Foot Cream
NDC: 73076-201 | Form: CREAM
Manufacturer: Shenzhen Ishan Technology Co., Ltd
Category: homeopathic | Type: HUMAN OTC DRUG LABEL
Date: 20260213

ACTIVE INGREDIENTS: OATMEAL 1 g/100 g
INACTIVE INGREDIENTS: WATER; STELLERA CHAMAEJASME WHOLE 5 g/100 g; PHELLODENDRON CHINENSE WHOLE 3 g/100 g; MAGNOLIA SIEBOLDII ROOT 3 g/100 g; MENTHOL 1 g/100 g; BASSIA SCOPARIA FRUIT 3 g/100 g; DICTAMNUS DASYCARPUS ROOT 3 g/100 g; SOPHORA FLAVESCENS ROOT 5 g/100 g

Active ingredients

Clotrimazole----1%----Antifungal

Inactive ingredients

Purify water, dictamnus dasycarpus root, sophora flavescens root, phellodendron chinense whole, menthol, magnolia sieboldii root, bassia scoparia fruit, stellera chamaejasme whole.

Keep out of reach of children.

if swallowed, call poison control or seek medical help.

Ask a doctor before

using on children under 2 years of age.

Stop use and ask a doctor if

Irritation occurs & condition persists or there is no improvementof athlete's foot or ringworm within 4 weeks or jock itch with 2 weeks.

USES

Cures most athlete's foot (tinea pedis), jock itch (tinea cruris), ringworm (tinea corporis). For effective relief of itching, burning, cracking, irritation, scaling and discomforts which accompany these conditions.

Other information

Store between 15℃ and 30℃ (50℉ and 86℉)

Directions

* Clean the affected area and dry thoroughly
* Apply a thin layer of LMNOOP over affected area twice daily (morning and night) or as directed by a doctor.
* Use daily for 4 weeks, pay special attention to the spaces between the toes; wear well-fitting ventilated shoes, and change shoes and socks at least once daily.
* Supervise children in the use of this product.
* Wash hands after each use.

Dosage & administration

Apply as needed

When Using this product

do not get into eyes. Do not use on nails or scalp & near the mouth or the eyes area.

Warning

For external use only.